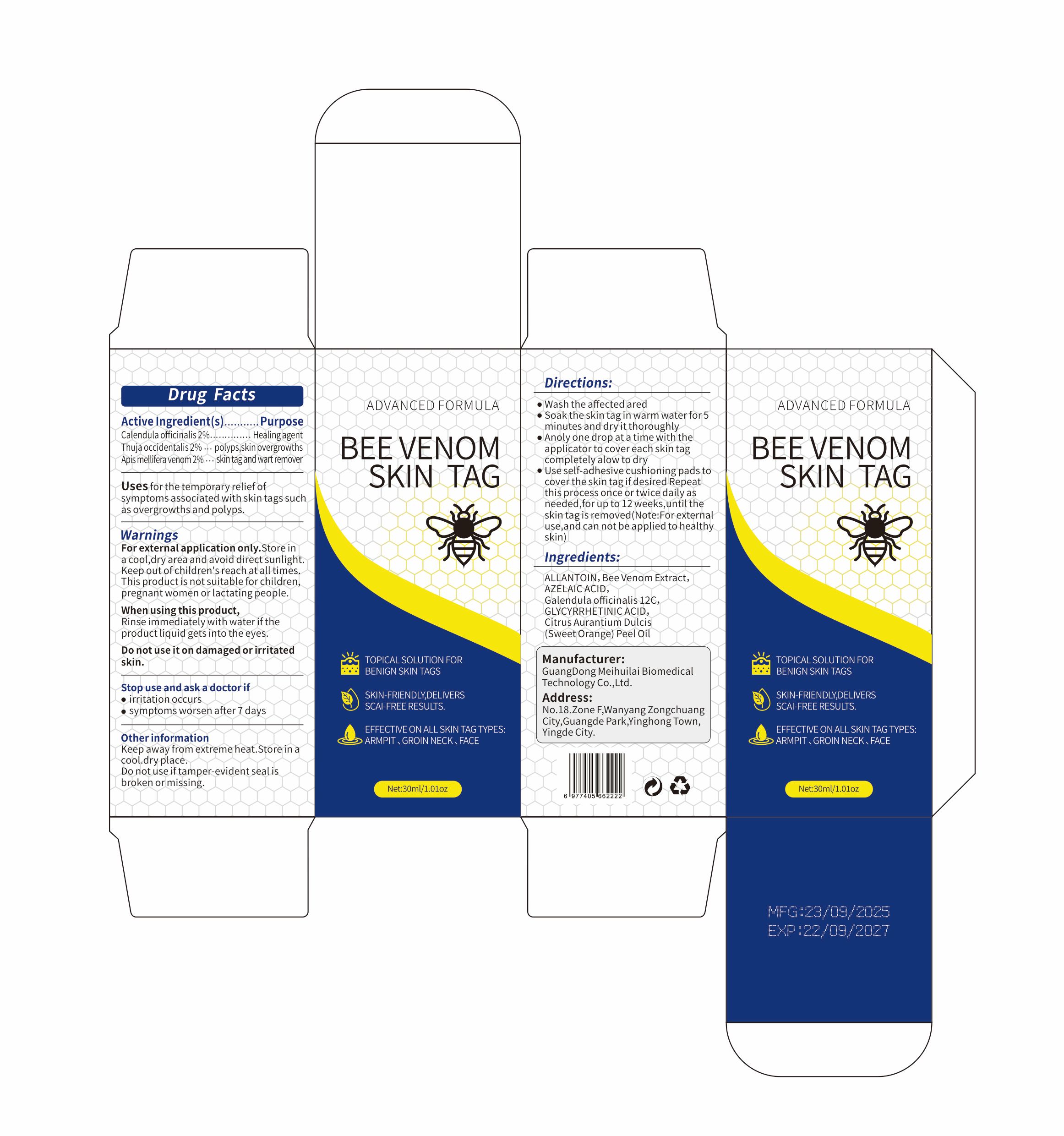 DRUG LABEL: BEE VENOM SKIN TAG
NDC: 85593-116 | Form: LIQUID
Manufacturer: Guangzhou ChuanMa International Trading Co.,Ltd.
Category: otc | Type: HUMAN OTC DRUG LABEL
Date: 20251102

ACTIVE INGREDIENTS: APIS MELLIFERA VENOM 2 g/100 mL; THUJA OCCIDENTALIS WHOLE 2 g/100 mL; CALENDULA OFFICINALIS FLOWERING TOP 2 g/100 mL
INACTIVE INGREDIENTS: CALENDULA OFFICINALIS SEED OIL; CITRUS AURANTIUM DULCIS (ORANGE) PEEL POWDER; ALLANTOIN; GLYCYRRHETINIC ACID; AZELAIC ACID

ACTIVE INGREDIENT

Calendula officinalis2% Thuja occidentalis2% Apis mellifera venom 2%

KEEP OUT OF REACH OF CHILDREN

This product is not suitable for children,pregnant women or lactating people. keep out of reach of children

PURPOSE

Uses for the temporary reliefofsymptoms associated with skin tags suchas overgrowths and polyps

DOSAGE AND ADMINISTRATION

Wash the affected aredSoak the skin tagin warm water for 5minutes and dryit thoroughlyAnoly one drop at a time with theapplicator to cover each skin tagcompletely alow to dryUse self-adhesive cushioning pads tocover the skin tagif desired Repeatthis process once or twice daily asneeded,for up to 12 weeks,until theskin tagis removed(Note:For externaluse,and can not be applied to healthyskin)

INDICATIONS AND USAGE

For external application only.

INACTIVE INGREDIENT

ALLANTOlN, Bee Venom Extract,AZELAIC ACID,Galendula officinalis 12C,GLYCYRRHETINIC ACID,Citrus Aurantium Dulcis(SweetOrange) Peel Oil

When using this product,Rinseimmediately with wateriftheproduct liquid gets into the eyesDo not use it on damaged orirritatedskin.
Stop use and ask a doctorifirritation occurssymptoms worsen after7 days